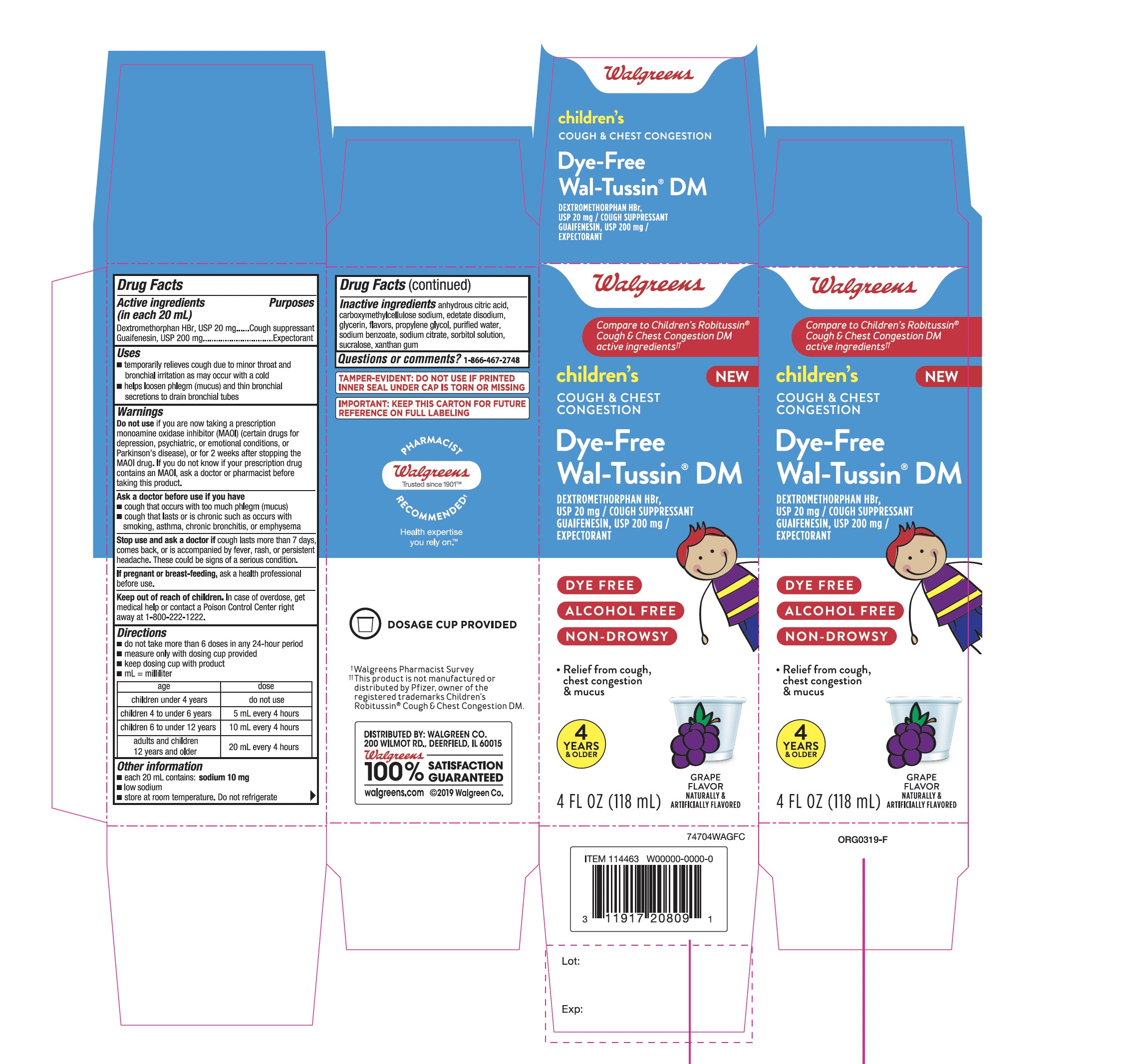 DRUG LABEL: Walgreens

NDC: 0363-7470 | Form: LIQUID
Manufacturer: WALGREENS
Category: otc | Type: HUMAN OTC DRUG LABEL
Date: 20251126

ACTIVE INGREDIENTS: DEXTROMETHORPHAN HYDROBROMIDE 20 mg/20 mL; GUAIFENESIN 200 mg/20 mL
INACTIVE INGREDIENTS: ANHYDROUS CITRIC ACID; CARBOXYMETHYLCELLULOSE SODIUM, UNSPECIFIED; EDETATE DISODIUM; GLYCERIN; PROPYLENE GLYCOL; WATER; SODIUM BENZOATE; SODIUM CITRATE, UNSPECIFIED FORM; SORBITOL; SUCRALOSE; XANTHAN GUM

Walgreens Children’s Cough& Chest Congestion Grape Flavor

Active ingredients (in each 20 mL)

Dextromethorphan HBr, USP 20 mg
Guaifenesin, USP 200 mg

Purposes

Cough suppressant
Expectorant

Uses

- temporarily relieves cough due to minor throat and bronchial irritation as may occur with a cold
- helps loosen phlegm (mucus) and thin bronchial secretions to drain bronchial tubes

Do not use

If your are now taking a prescription monoamine oxidase inhibitor (MAOI) (certain drugs for depression, psychiatric, or emotional conditions, or Parkinson's disease), or for 2 weeks after stopping the MAOI drug. If you do not know if your child's prescription drug contains an MAOI, ask a doctor or pharmacist before taking this product.

Ask a doctor before use if you have

- cough that occurs with too much phlegm (mucus)
- cough that lasts or is chronic such as occurs with smoking, asthma, chronic bronchitis, or emphysema

Stop use and ask a doctor if

cough lasts more than 7 days, comes back, or is accompanied by fever, rash, or persistent headache. These could be signs of a serious condition.

If pregnant or breast-feeding,

ask a health professional before use.

Keep out of reach of children.

In case of overdose, get medical help or contact a Poison Control Center right away at (1-800-222-1222).

Directions

- do not take more than 6 doses in any 24-hour period
- measure only with dosing cup provided
- keep dosing cup with product
- mL = milliliter

Age | Dose
children under 4 years | do not use
children 4 to under 6 years | 5 mL every 4 hours
children 6 to under 12 years | 10 mL every 4 hours
adults and children 12 years and older | 20 mL every 4 hours

Other information

- each 20 mL contains: sodium 10 mg
- low sodium
- store at room temperature. Do not refrigerate.

Inactive ingredients

anhydrous citric acid, carboxymethylcellulose sodium, edetate disodium, glycerin, flavor, propylene glycol, purified water, sodium benzoate, sodium citrate, sorbitol solution, sucralose, xanthan gum.

Questions or Comments

1-866-467-2748

PACKAGE LABEL-PRINCIPAL DISPLAY PANEL - 4 FL OZ (118 mL Bottle)

Walgreens

Compare to the Children's Robitussin®Cough & Chest Congestion DM active ingredients††
NDC 0363-7470-04
Children'sCOUGH& CHESTCONGESTION
Dye-Free

Wal-Tussin®DM
DEXTROMETHORPHAN HBr,
USP 20 mg/COUGH SUPPRESSANT
GUAIFENESIN, USP 200 mg/EXPECTORANT

DYE FREE

ALCOHOL FREE

NON-DROWSY

- Relief from cough chest congestion & mucus

4 YEARS & OLDER
GRAPE FLAVOR

NATURALLY & ARTIFICIALLY FALVORED
4 FL OZ (118 mL)

TAMPER-EVIDENT: DO NOT USE IF PRINTED INNER SEAL UNDER CAP IS TORN OR MISSING

IMPORTANT: KEEP THIS CARTON FOR FUTURE REFERENCE ON FULL LABELING

†Walgreens Pharmacist Survey

††This product is not manufactured or distributed by Pfizer, owner of the registered trademarks Children’s Robitussin®Cough & Chest Congestion DM.

DISTRIBUTED BY: WALGREEN CO.

200 WILMOT RD., DEERFIELD, IL 60015

Walgreens

100% SATISFACTION GUARANTEED

Walgreens.com ©2019 Walgreen Co.